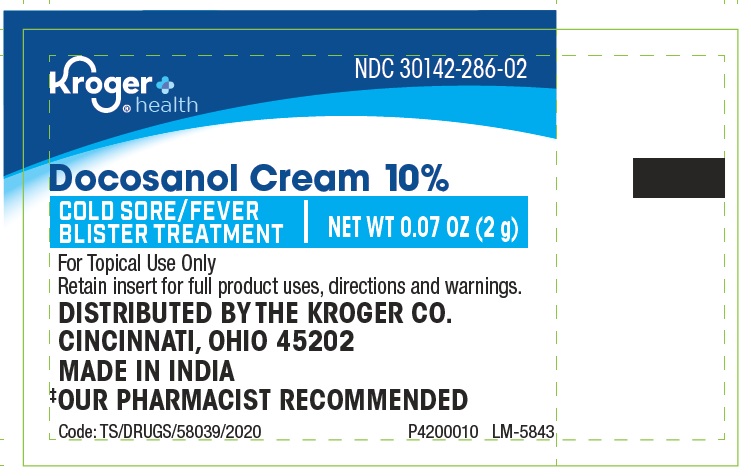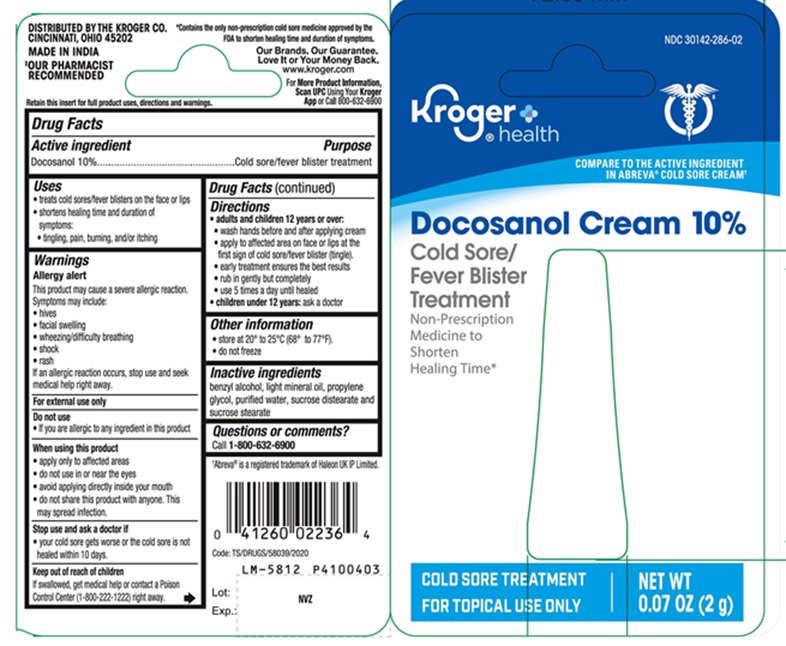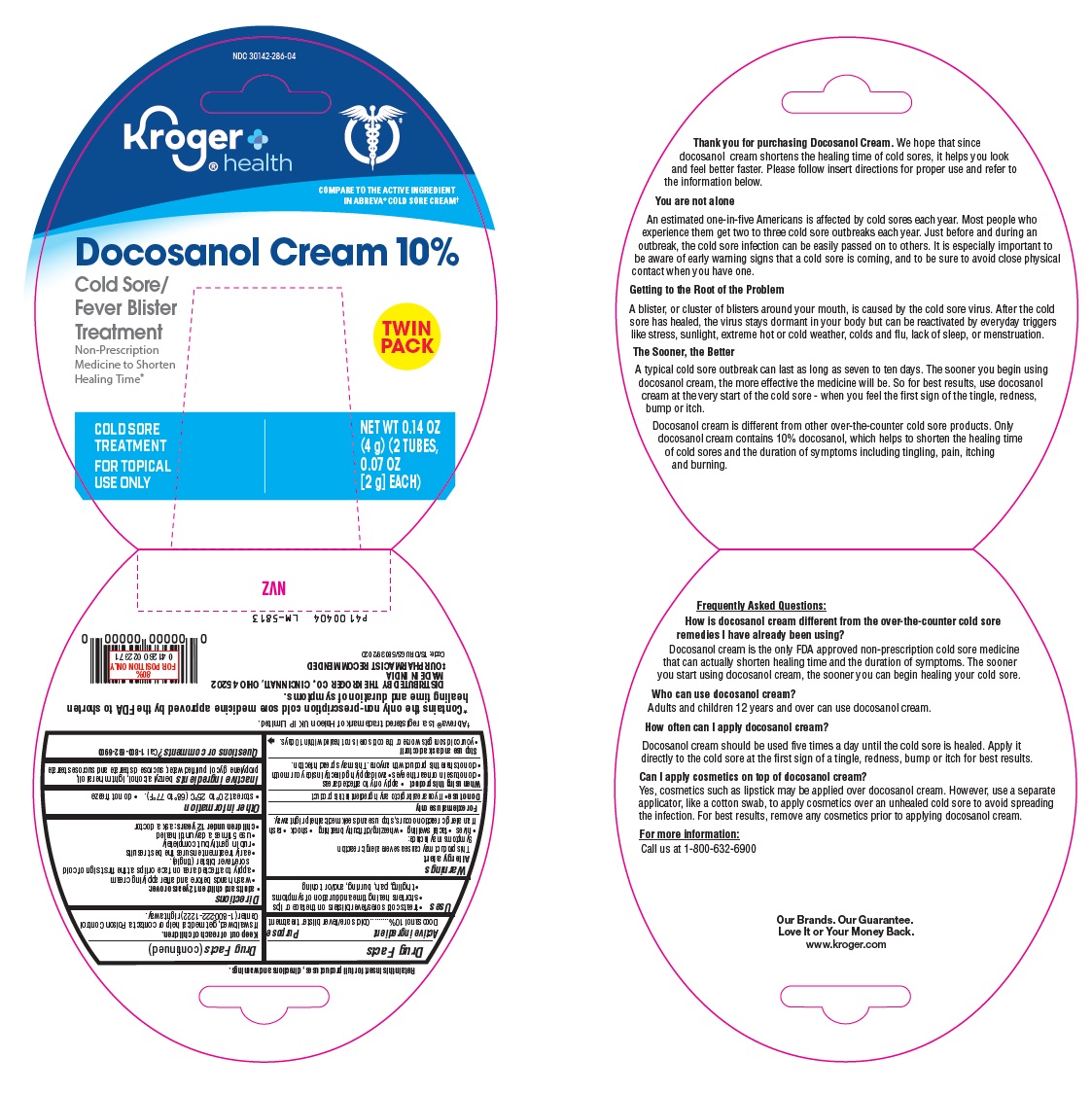 DRUG LABEL: DOCOSANOL
NDC: 30142-286 | Form: CREAM
Manufacturer: KROGER COMPANY
Category: otc | Type: Human OTC Drug Label
Date: 20251211

ACTIVE INGREDIENTS: DOCOSANOL 100 mg/1 g
INACTIVE INGREDIENTS: BENZYL ALCOHOL; LIGHT MINERAL OIL; PROPYLENE GLYCOL; WATER; SUCROSE DISTEARATE; SUCROSE STEARATE

Drug Facts

Active ingredient

Docosanol 10%

Purpose

Cold sore/fever blister treatment

Uses

- treats cold sores/fever blisters on the face or lips
- shortens healing time and duration of symptoms:
  - tingling, pain, burning, and/or itching

Warnings

Allergy alert

This product may cause a severe allergic reaction. Symptoms may include:

• hives

• facial swelling

• wheezing/difficulty breathing

• shock

• rash

If an allergic reaction occurs, stop use and seek medical help right away.

For external use only

Do not use

• If you are allergic to any ingredient in this product

When using this product

• apply only to affected areas

• do not use in or near the eyes

• avoid applying directly inside your mouth

• do not share this product with anyone. This may spread infection.

Stop use and ask a doctor if

• your cold sore gets worse or the cold sore is not healed within 10 days.

Keep out of reach of children

If swallowed, get medical help or contact a Poison Control Center (1-800-222-1222) right away.

Directions

• adults and children 12 years or over:

• wash hands before and after applying cream

• apply to affected area on face or lips at the first sign of cold sore/fever blister (tingle).

• early treatment ensures the best results

• rub in gently but completely

• use 5 times a day until healed

• children under 12 years: ask a doctor

Other information

• store at 20° to 25°C (68° to 77°F).

• do not freeze

Inactive ingredients

benzyl alcohol, light mineral oil, propylene glycol, purified water, sucrose distearate and sucrose stearate

Questions or comments?

call 1-800-632-6900

Additional information

*Contains the only non-prescription cold sore medicine approved by the FDA to shorten healing time and duration of symptoms.

Retain insert for full product uses, directions and warnings.
DISTRIBUTED BY
THE KROGER CO., CINCINNATI, OHIO 45202
MADE IN INDIA
‡OUR PHARMACIST RECOMMENDED
Code: TS/DRUGS/58039/2020

Thank you for purchasing Docosanol Cream. We hope that since docosanol cream shortens the healing time of cold sores, it helps you look and feel better faster. Please follow insert directions for proper use and refer to the information below.

You are not alone

An estimated one-in-five Americans is affected by cold sores each year. Most people who experience them get two to three cold sore outbreaks each year. Just before and during an outbreak, the cold sore infection can be easily passed on to others. It is especially important to be aware of early warning signs that a cold sore is coming, and to be sure to avoid close physical contact when you have one.

Getting to the Root of the Problem

A blister, or cluster of blisters around your mouth, is caused by the cold sore virus. After the cold sore has healed, the virus stays dormant in your body but can be reactivated by everyday triggers like stress, sunlight, extreme hot or cold weather, colds and flu, lack of sleep, or menstruation.

The Sooner, the Better

A typical cold sore outbreak can last as long as seven to ten days. The sooner you begin using docosanol cream, the more effective the medicine will be. So for best results, use docosanol cream at the very start of the cold sore - when you feel the first sign of the tingle, redness, bump or itch.
Docosanol cream is different from other over-the-counter cold sore products. Only docosanol cream contains 10% docosanol, which helps to shorten the healing time of cold sores and the duration of symptoms including tingling, pain, itching and burning.
Frequently Asked Questions:
How is docosanol cream different from the over-the-counter cold sore remedies I have already been using?
Docosanol cream is the only FDA approved non-prescription cold sore medicine that can actually shorten healing time and the duration of symptoms. The sooner you start using docosanol cream, the sooner you can begin healing your cold sore.

Who can use docosanol cream?

Adults and children 12 years and over can use docosanol cream.

How often can I apply docosanol cream?

Docosanol cream should be used five times a day until the cold sore is healed. Apply it directly to the cold sore at the first sign of a tingle, redness, bump or itch for best results.

Can I apply cosmetics on top of docosanol cream?

Yes, cosmetics such as lipstick may be applied over docosanol cream. However, use a separate applicator, like a cotton swab, to apply cosmetics over an unhealed cold sore to avoid spreading the infection. For best results, remove any cosmetics prior to applying docosanol cream.

For more information:
Call us at 1-800-632-6900

PACKAGE LABEL-PRINCIPAL DISPLAY PANEL - Tube Label 10% (2 g Tube)

NDC 30142-286-02

Kroger®
health

Docosanol Cream 10%
COLD SORE / FEVER
BLISTER TREATMENT
NET WT 0.07 0Z (2g)
For Topical Use Only

PACKAGE LABEL-PRINCIPAL DISPLAY PANEL - Tube Square Blister Card Label 10% (2 g Tube)

NDC 30142-286-02
Kroger®
health
COMPARE TO THE ACTIVE INGREDIENT
IN ABREVA® COLD SCORE CREAM†
Docosanol Cream 10%
Cold Sore/
Fever Blister
Treatment
Non-Prescription
Medicine to
Shorten
Healing Time*
COLD SORE TREATMENT
FOR TOPICAL USE ONLY
NET WT
0.07 oz (2 g)

PACKAGE LABEL-PRINCIPAL DISPLAY PANEL - Tube Clamshell Blister Card label 10% (2 g Tube)

NDC 30142-286-04
Kroger®
health
COMPARE TO THE ACTIVE INGREDIENT
IN ABREVA® COLD SCORE CREAM†
Docosanol Cream 10%
Cold Sore/
Fever Blister
Treatment TWIN
Non-Prescription PACK
Medicine to
Shorten
Healing Time*
COLD SORE
TREATMENT
FOR TOPICAL
USE ONLY
NET WT 0.14 OZ
(4 g) (2 TUBES,
0.07 OZ
[2 g] EACH)